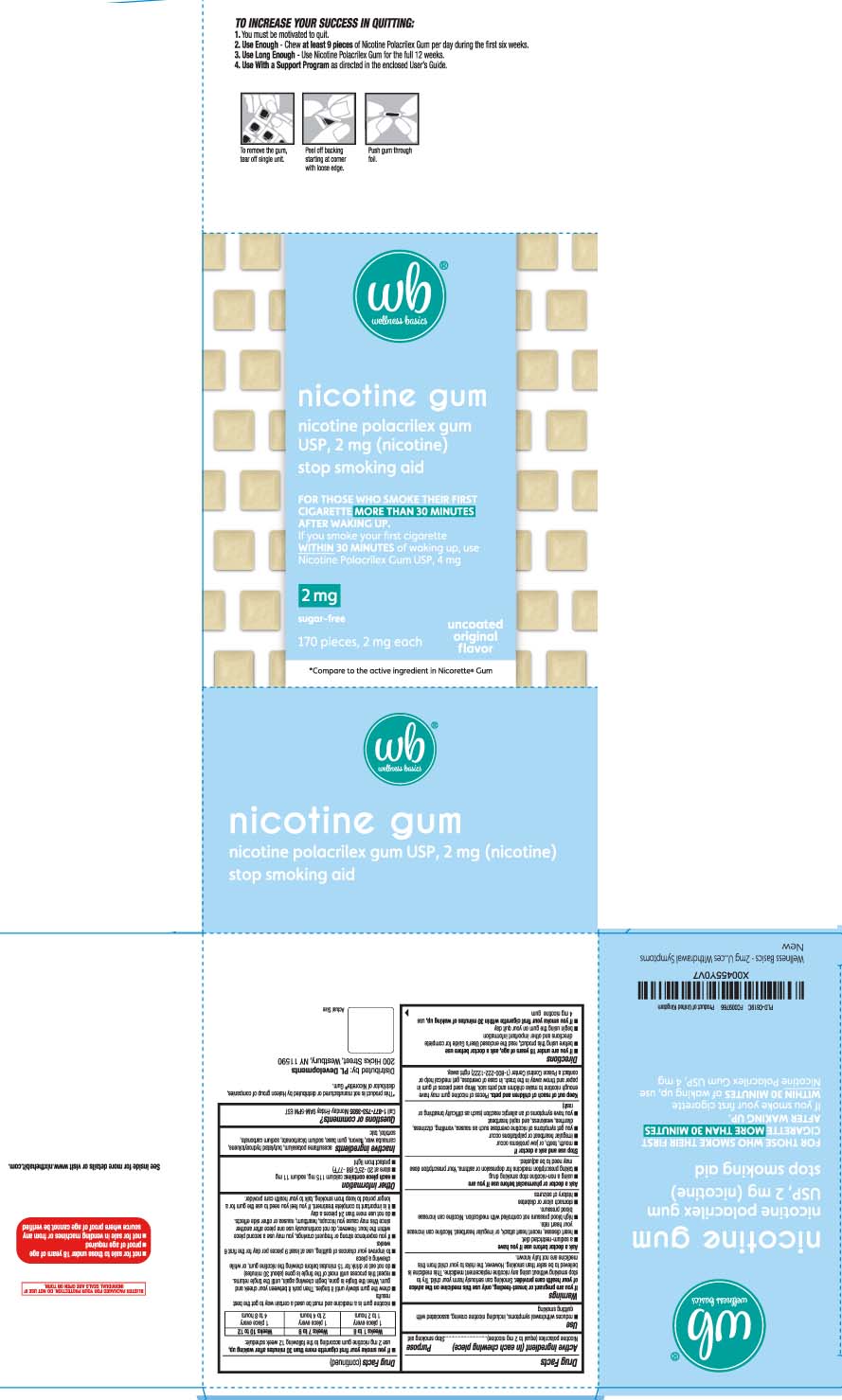 DRUG LABEL: Nicotine
NDC: 59726-929 | Form: GUM, CHEWING
Manufacturer: P & L Development, LLC
Category: otc | Type: HUMAN OTC DRUG LABEL
Date: 20260227

ACTIVE INGREDIENTS: NICOTINE 2 mg/1 1
INACTIVE INGREDIENTS: ACESULFAME POTASSIUM; BUTYLATED HYDROXYTOLUENE; CARNAUBA WAX; SODIUM BICARBONATE; SODIUM CARBONATE; TALC; SORBITOL

Drug Facts

Active ingredient (in each chewing piece)

Nicotine polacrilex (equal to 2 mg nicotine)

Purpose

Stop smoking aid

Use

- reduces withdrawal symptoms, including nicotine craving, associated with quitting smoking

Warnings

If you are pregnant or breast-feeding,

only use this medicine on the advice of your health care provider. Smoking can seriously harm your child. Try to stop smoking without using any nicotine replacement medicine. This medicine is believed to be safer than smoking. However, the risks to your child from this medicine are not fully known.

Ask a doctor before use if you have

- a sodium-restricted diet
- heart disease, recent heart attack, or irregular heartbeat. Nicotine can increase your heart rate.
- high blood pressure not controlled with medication. Nicotine can increase your blood pressure.
- stomach ulcer or diabetes
- history of seizures

Ask a doctor or pharmacist before use if you are

- using a non-nicotine stop smoking drug
- taking prescription medicine for depression or asthma. Your prescription dose may need to be adjusted.

Stop use and ask a doctor if

- mouth, teeth, or jaw problems occur
- irregular heartbeat or palpitations occur
- you get symptoms of nicotine overdose such as nausea, vomiting, dizziness, diarrhea, weakness and rapid heartbeat
- you have symptoms of an allergic reaction (such as difficulty breathing or rash)

Keep out of reach of children and pets.

Pieces of nicotine gum may have enough nicotine to make children and pets sick. Wrap used pieces of gum in paper and throw away in the trash. In case of overdose, get medical help or contact a Poison Control Center (1-800-222-1222) right away.

Directions

- if you are under 18 years of age, ask a doctor before use
- before using this product, read the enclosed User’s Guide for complete directions and other important information
- begin using the gum on your quit day
- if you smoke your first cigarette within 30 minutes of waking up, use 4 mg nicotine gum
- if you smoke your first cigarette more than 30 minutes after waking up, use 2 mg nicotine gum according to the following 12 week schedule

Weeks 1 to 6 | Weeks 7 to 9 | Weeks 10 to 12
1 piece every 1 to 2 hours | 1 piece every 2 to 4 hours | 1 piece every 4 to 8 hours

- nicotine gum is a medicine and must be used a certain way to get the best results
- chew the gum slowly until it tingles. Then park it between your cheek and gum. When the tingle is gone, begin chewing again, until the tingle returns.
- repeat the process until most of the tingle is gone (about 30 minutes)
- do not eat or drink 15 minutes before chewing the nicotine gum, or while chewing a piece
- to improve your chances of quitting, use at least 9 pieces per day for the first 6 weeks
- if you experience strong or frequent cravings, you may use a second piece within the hour. However, do not continuously use one piece after another since this may cause you hiccups, heartburn, nausea or other side effects.
- do not use more than 24 pieces a day
- It is important to complete treatment. If you feel you need to use the gum for a longer period to keep from smoking, talk to your health care provider.

Other information

- each piece contains: calcium 115 mg, sodium 11 mg
- store at 20-25ºC (68-77ºF)
- protect from light

Inactive ingredients

acesulfame potassium, butylated hydroxytoluene, carnauba wax, flavors, gum base, sodium bicarbonate, sodium carbonate, sorbitol, talc

Questions or comments?

Call 1-877-753-3935 Monday-Friday 9AM-5PM EST

Principal Display Panel

*Compare to the active ingredient of Nicorette® Gum

nicotine gum

nicotine polacrilex gum USP, 2 mg (nicotine)

stop smoking aid

FOR THOSE WHO SMOKE THEIR FIRST CIGARETTE MORE THAN 30 MINUTES AFTER WAKING UP.

If you smoke your first cigarette WITHIN 30 MINUTES of waking up, use Nicotine Polacrilex Gum USP, 4 mg

uncoated original flavor

TO INCREASE YOUR SUCCESS IN QUITTING:

1. You must be motivated to quit.

2. Use Enough - Use at least 9 Nicotine Polacrilex Gum per day during the first six weeks.

3. Use Long Enough - Use Nicotine Polacrilex Gum for the full 12 weeks.

4. Use With a Support Program as directed in the enclosed User's Guide.

To remove the gum, tear off single unit.

Peel off backing starting at corner with loose edge.

Push gum through foil

- not for sale to those under 18 years of age
- proof of age required
- not for sale in vending machines or from any source where proof of age cannot be verified

*This product is not manufactured or distributed by Haleon group of companies, distributor of Nicorette® Gum

See inside for more details or visit www.nitthehabit.com

BLISTER PACKAGED FOR YOUR PROTECTION. DO NOT USE IF INDIVIDUAL SEALS ARE OPEN OR TORN

Distributed by: PL Developments

200 Hicks Street, Westbury, NY 11590

Package Label

WELLNESS BASICS Sugar Free Nicotine Polacrilex Uncoated Original Flavor